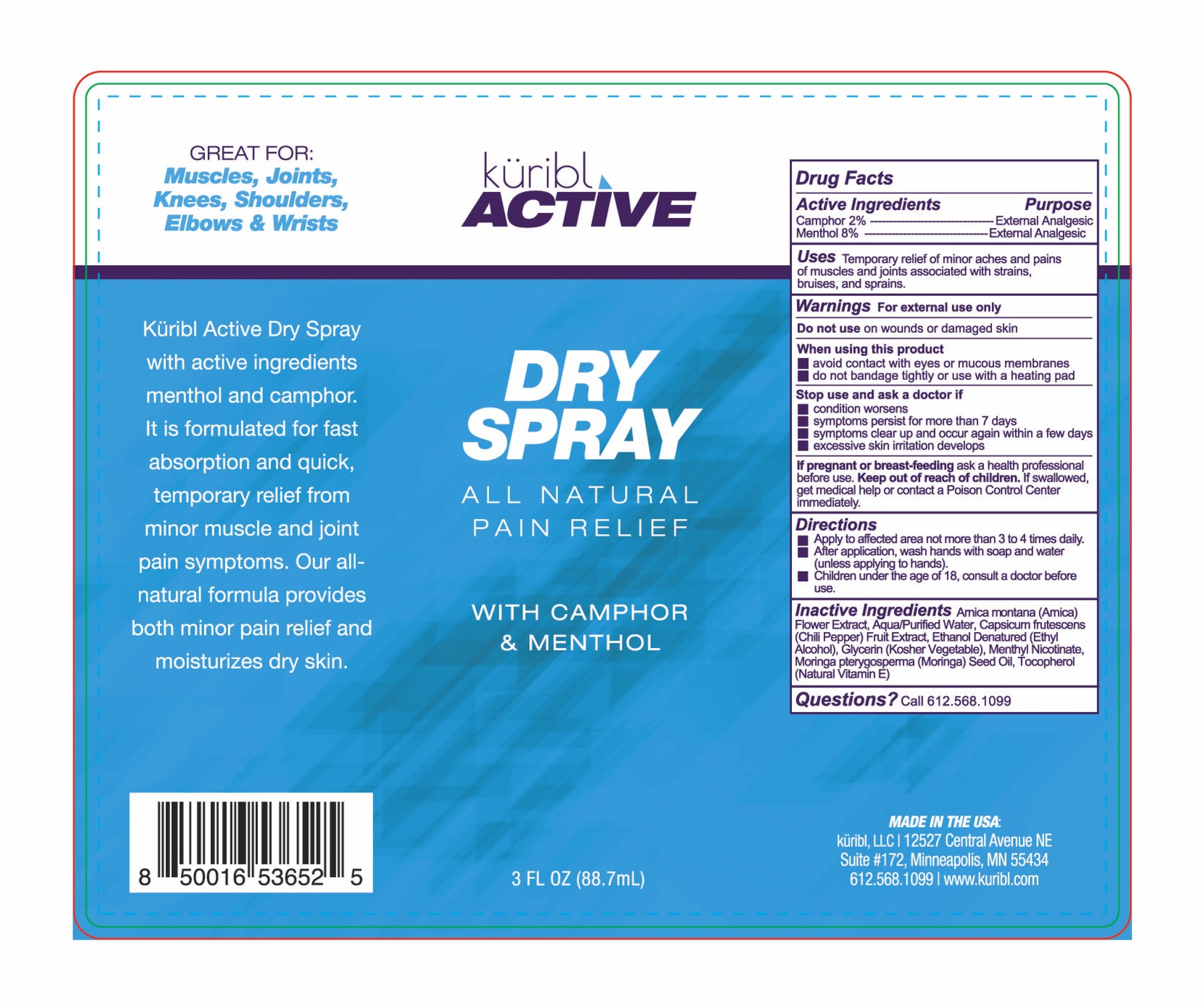 DRUG LABEL: Kuribl Active Dry
NDC: 83111-002 | Form: CREAM
Manufacturer: Radiance Beauty & Wellness Inc. dba Saavy Naturals
Category: otc | Type: HUMAN OTC DRUG LABEL
Date: 20230127

ACTIVE INGREDIENTS: MENTHOL 8 g/100 mL; CAMPHOR (NATURAL) 2 g/100 mL
INACTIVE INGREDIENTS: ARNICA MONTANA FLOWER; MORINGA OLEIFERA SEED OIL; WATER; TABASCO PEPPER; ALCOHOL; GLYCERIN; TOCOPHEROL

Kuribl Active Dry Spray

Active Ingredients Purpose

Camphor 2% External Analgesic

Menthol 8% External Analgesic

PURPOSE

Uses Temporary relief of minor aches and pains of muscles and joints associated with strains, bruises and sprains.

Keep out of reach of children. If swallowed, get medical help or contact a Poison Control Center immediately.

Stop use and ask a doctor if

- condition worsens
- symptoms persist for more than 7 days
- symptoms clear up and occur again within a few days
- excessive skin irritation develops

Warnings For external use only

Do not use on wounds or damaged skin

When using this product

- avoid contact with eyes or mucous membranes
- do not bandage tightly or use with a heating pad

If pregnant or breast-feeding ask a health professional before use

Directions

- Apply to affected area not more than 3 to 4 times daily.
- After application, wash hands with soap and water (unless applying to hands)
- Children under the age of 18, consult a doctor before use

INACTIVE INGREDIENT

Inactive ingredients Arnica Montana (Arnica) Flower Extract, Aqua/Purified Water, Capsicum Frutescens (Chili Pepper) Fruit Extract, Ethanol Denatured (Ethyl Alcohol), Glycerin (Kosher Vegetable), Menthyl Nicotinate, Moringa pterygosperma (Moringa) Seed Oil, Tocopherol (Natural Vitamin E)

PACKAGE LABEL

Kuribl Active

Dry Spray

All Natural Pain Relief

With Camphor & Menthol

3 FL OZ (88.7 mL)